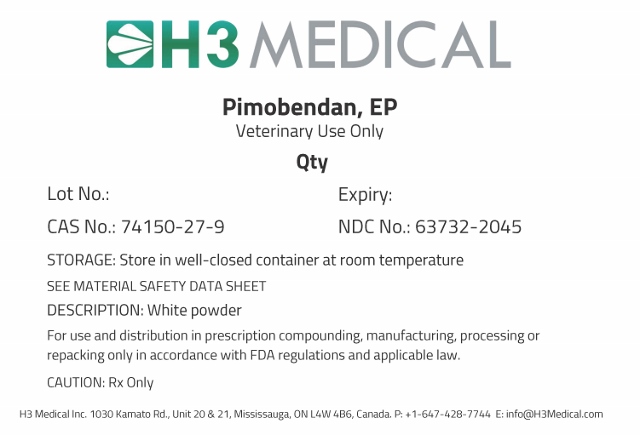 DRUG LABEL: Pimobendan
NDC: 63732-2045 | Form: POWDER
Manufacturer: H3 Medical Inc.
Category: other | Type: BULK INGREDIENT
Date: 20190905

ACTIVE INGREDIENTS: PIMOBENDAN 1 g/1 g

Pimobendan